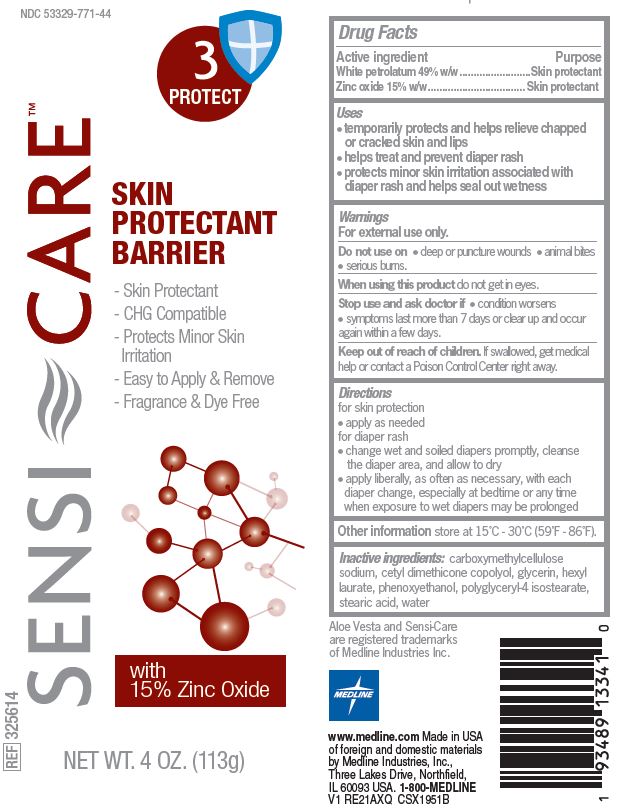 DRUG LABEL: Sensi-Care
NDC: 53329-771 | Form: CREAM
Manufacturer: Medline Industries, LP
Category: otc | Type: HUMAN OTC DRUG LABEL
Date: 20240702

ACTIVE INGREDIENTS: ZINC OXIDE 15 g/100 g; PETROLATUM 49 g/100 g
INACTIVE INGREDIENTS: WATER; GLYCERIN; CARBOXYMETHYLCELLULOSE SODIUM, UNSPECIFIED; PHENOXYETHANOL; POLYGLYCERYL-4 ISOSTEARATE; STEARIC ACID

771 Sensi-Care Protective Barrier

Active ingredient

White petrolatum 49% w/w

Zinc oxide 15% w/w

Purpose

Skin protectant

Uses

- temporarily protects and helps relieve chapped or cracked skin and lips
- helps treat and prevent diaper rash
- protects minor skin irritation associated with diaper rash adn helps seal out wetness

Warnings

For external use only.

Do not use on

- deep or puncture wounds
- animal bites
- serious burns

When using this product

do not get in eyes

Stop use and ask doctor if

- condition worsens
- symptoms last more than 7 days or clear up and occur again within a few days

Keep out of reach of children.

If swallowed, get medical help or contact a Poison Control Center right away.

Directions

for skin protection:

- apply as needed

for diaper rash:

- change wet and soiled diapers promptly, cleans the diaper area, and allow to dry
- apply liberally, as often as necessary, with each diaper change, especially at bedtime or anytime when exposure to wet diapers may be prolonged

Other information

- store at 15°C-30°C (59°F-86°F)

Inactive ingredients

carboxymethylcellulose sodium, cetyl dimethicone copolyol, glycerin, hexyl laurate, phenoxyethanol, polyglyceryl-4 isostearate, stearic acid, water

Manufacturing Information

Manufactured for: Medline Industries, LP

Three Lakes Drive, Northfield, IL 60093 USA

Made in USA with foreign and domestic materials

www.medline.com

1-800-MEDLINE

REF: 325614

V1 RE21AXQ